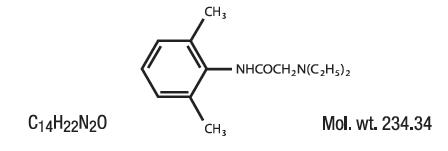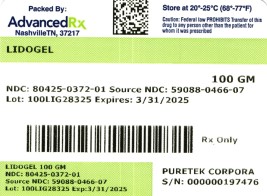 DRUG LABEL: Lidogel
NDC: 80425-0372 | Form: GEL
Manufacturer: Advanced Rx Pharmacy of Tennessee, LLC
Category: prescription | Type: HUMAN PRESCRIPTION DRUG LABEL
Date: 20240118

ACTIVE INGREDIENTS: LIDOCAINE HYDROCHLORIDE 28 mg/1 g
INACTIVE INGREDIENTS: PROPYLENE GLYCOL; WATER; HYDROXYETHYL CELLULOSE, UNSPECIFIED; METHYLPARABEN; PROPYLPARABEN; POLYETHYLENE GLYCOL 200; ALOE VERA LEAF; ANHYDROUS CITRIC ACID

Lidogel

DESCRIPTION

Contains Lidocaine HCl 2.8% in a mild acidic vehicle. Lidocaine is chemically designated as acetamide, 2-(diethylamino)-N-(2,6-dimethylphenyl), and has the following structure:

INGREDIENTS:Each gram of Lidogel™ 2.8% Gelcontains Lidocaine HCl USP 28 mg. Inactive Ingredients include: Aloe Barbadensis (Aloe Vera) Leaf Juice, Citric Acid, Hydroxyethylcellulose, Methylparaben, PEG-4, Propylene Glycol, Propylparaben, Purified Water.

CLINICAL PHARMACOLOGY:

MECHANISM OF ACTION:

Lidogel™ 2.8% Gelreleases Lidocaine from a mild acidic vehicle to stabilize the neuronal membrane by inhibiting the ionic fluxes
required for initiation and conduction of impulses, thereby affecting local anesthetic action. A mild acidic vehicle lowers pH to increase protection against alkaline irritants and to provide a favorable environment for healing.

PHARMACOKINETICS:

Lidocaine may be absorbed following topical administration to mucous membranes, its rate and extent of absorption depending upon the specific site of application, duration of exposure, concentration, and total dosage. In general, the rate of absorption of local anesthetic agents following topical application occurs most rapidly after intratracheal administration. Lidocaine is also well-absorbed from the gastrointestinal tract, but little intact drug appears in the circulation because of biotransformation in the liver.

Lidocaine is metabolized rapidly by the liver and metabolites and unchanged drugs are excreted by the kidneys. Biotransformation includes oxidative N-dealkylation, ring hydroxylation, cleavage of the amide linkage, and conjugation. N-dealkylation, a major pathway of biotransformation, yields the metabolites monoethylglycinexylidide and glycinexylidide. The pharmacological/toxicological actions of these metabolites are similar to but less potent than, those of Lidocaine. Approximately 90% of Lidocaine administered is excreted in the form of various metabolites and less than 10% is excreted unchanged. The primary metabolite in urine is a conjugate of 4-hydroxy-2, 6-dimethylaniline. The plasma binding of Lidocaine is dependent on drug concentration and the fraction bound decreases with increasing concentration. At concentrations of 1 to 4 g of free base per mL, 60 to 80 percent of Lidocaine is protein bound. Binding is also dependent on the plasma concentration of the alpha-1-acid glycoprotein. Lidocaine crosses the blood-brain and placental barriers, presumably by passive diffusion. Studies of Lidocaine metabolism following intravenous bolus injections have shown that the elimination half-life of this agent is typically 1.5 to 2 hours. Because of the rapid rate at which Lidocaine is metabolized, any condition that affects liver function may alter Lidocaine kinetics. The half-life may be prolonged two-fold or more in patients with liver dysfunction. Renal dysfunction does not affect Lidocaine kinetics but may increase the accumulation of metabolites. Factors such as acidosis and the use of CNS stimulants and depressants affect the CNS levels of Lidocaine required to produce overt systemic effects. Objective adverse manifestations become increasingly apparent with increasing venous plasma levels above 6 g free base per mL. In the rhesus monkey, arterial blood levels of 18-21 g/mL have been shown to be threshold for convulsive activity.

INDICATIONS:

For temporary relief of pain and itching associated with minor burns, sunburn, minor cuts, scrapes, insect bites, and minor skin irritation.

CONTRAINDICATIONS:

Tuberculous or fungal lesions of skin vaccinia, varicella, and acute herpes simplex and in persons who have shown hypersensitivity to any of its components. Lidocaine is contraindicated in patients with a known history of hypersensitivity to local anesthetics of the amide type.

WARNINGS:

For external use only. Not for ophthalmic use.
Keep out of reach of children.

PRECAUTIONS:

If irritation of sensitivity occurs or infection appears, discontinue use and institute appropriate therapy. Lidogel™ 2.8%Gel should
be used with caution in ill, elderly, debilitated patients and children who may be more sensitive to the systemic effects of Lidocaine.

CARCINOGENESIS, MUTAGENESIS, AND IMPAIRMENT OF FERTILITY:

Studies of Lidocaine in animals to evaluate the carcinogenic potential of the effect on fertility have not been conducted.

USE IN PREGNANCY

TERATOGENIC EFFECTS

Teratogenic Effects; Pregnancy Category B. Reproduction studies have been performed for Lidocaine in rats at doses up to 6.6 times the human dose and have revealed no evidence of harm to the fetus caused by Lidocaine. There are, however, no adequate and well-controlled studies in pregnant women. Animal reproduction studies are not always predictive of human response. General consideration should be given to this fact before administering Lidocaine to women of childbearing potential, especially during early pregnancy when maximum organogenesis takes place.

NURSING MOTHERS:

It is not known whether this drug is excreted in human milk. Because many drugs are excreted in human milk, caution should be
exercised when this drug is administered to a nursing mother.

PEDIATRIC USE:

Dosage in pediatric patients would be reduced commensurate with age, body weight, and physical condition.

ADVERSE REACTIONS:

During or immediately after treatment, the skin at the site of treatment may develop erythema or edema or may be the locus of
abnormal sensation.

DOSAGE AND ADMINISTRATION:

Apply a thin film to the affected area two or three times daily or as directed by a physician.

HOW SUPPLIED:

Lidogel 2.8% Gel 3.5 oz. (100 g) tube - NDC 80425-0372-01

KEEP THIS AND ALL MEDICATIONS OUT OF REACH OF CHILDREN.

STORAGE AND HANDLING:

Store at 20°-25°C (68°-77° F) [see USP Controlled Room Temperature]. Protect from freezing.